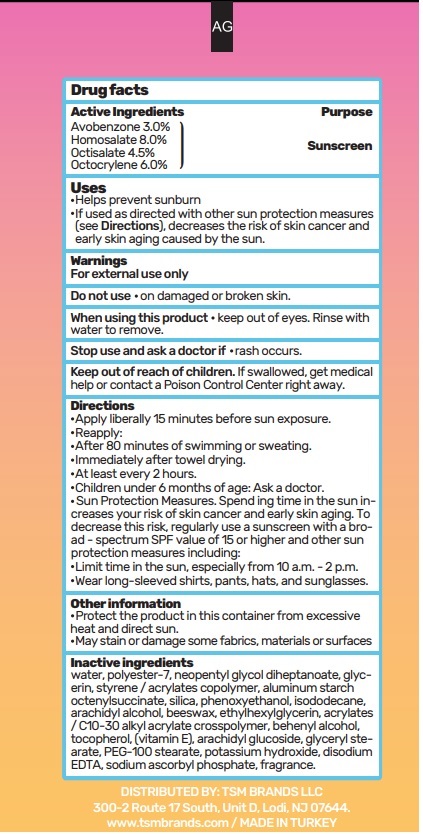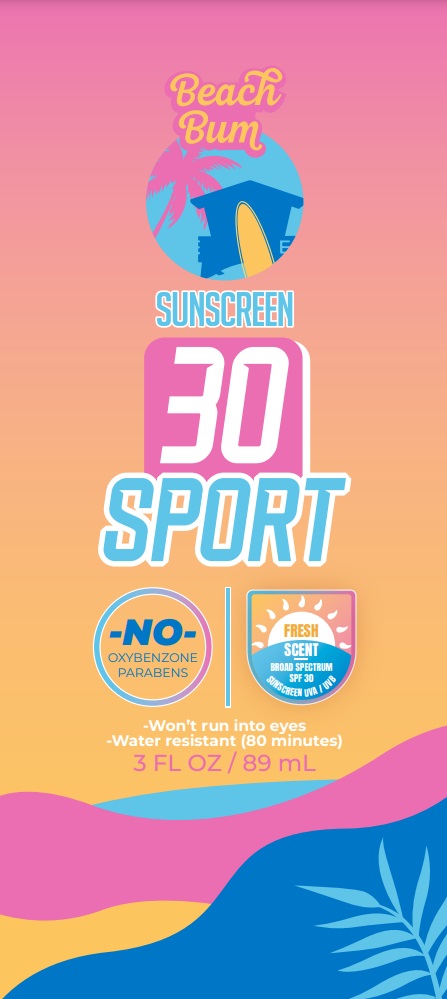 DRUG LABEL: BEACH BUM 30SPF SUNSCREEN 3FL OZ
NDC: 76567-9876 | Form: LOTION
Manufacturer: TSM BRANDS LLC
Category: otc | Type: HUMAN OTC DRUG LABEL
Date: 20250228

ACTIVE INGREDIENTS: AVOBENZONE 2.67 g/89 mL; OCTISALATE 4.005 g/89 mL; OCTOCRYLENE 5.34 g/89 mL; HOMOSALATE 7.12 g/89 mL
INACTIVE INGREDIENTS: GLYCERIN 2.67 mL/89 mL; STYRENE/ACRYLAMIDE COPOLYMER (MW 500000) 0.445 mL/89 mL; EDTA 0.089 mL/89 mL; ARACHIDYL ALCOHOL 1.246 mL/89 mL; BEHENYL ALCOHOL 0.356 mL/89 mL; SODIUM ASCORBYL PHOSPHATE 0.089 mL/89 mL; TOCOPHEROL 0.089 mL/89 mL; BEESWAX 1.78 mL/89 mL; ETHYLHEXYLGLYCERIN 0.0445 mL/89 mL; ISODODECANE 0.089 mL/89 mL; HYDRATED SILICA 0.001 mL/89 mL; ALUMINUM STARCH OCTENYLSUCCINATE 0.089 mL/89 mL; PHENOXYETHANOL 0.4 mL/89 mL; ACRYLATES/C10-30 ALKYL ACRYLATE CROSSPOLYMER (60000 MPA.S AT 0.5%) 0.1335 mL/89 mL; AQUA 58.177 mL/89 mL; GLYCERYL STEARATE/PEG-100 STEARATE 3 mL/89 mL; POTASSIUM HYDROXIDE 0.01 mL/89 mL; FRAGRANCE 13576 0.445 mL/89 mL; POLYESTER-7 0.2225 mL/89 mL; NEOPENTYL GLYCOL DIHEPTANOATE 0.2225 mL/89 mL; ARACHIDYL GLUCOSIDE 0.178 mL/89 mL

BEACH BUM SUNSCREEN

ACTIVE INGREDIENTS

Avobenzone 3.0%

Homosalate 8.0%

Octisalate 4.5%

Octocrylene 6.0%

Sunscreen

USES

Helps prevent sunburn

If used as directed with other sun protection measures (see Directions), decreases the risk of skin cancer and early skin aging caused by the sun.

Do not use on damaged or broken skin.

WHEN USING

When using this product, keep out of eyes. Rinse with water to remove.

STOP USE

Stop use and as a doctor if rash occurs

ASK A DOCTOR

Stop use and ask a doctor if rash occurs.

Keep out of reach of children. If swallowed, get medical help or contact a Poison Control Center right away.

INACTIVE INGREDIENTS

water, polyester-7, neopentyl glycol diheptanoate, glycerin, styrene/acrylates copolymer, alimunim starch octenylsuccinate, silica, pheoxyethanol, isododecane, arachidyl alcohol, beeswax, ethylhexyglycerin, acrylates/C10-30 akyl acrylate crosspolymer, behenyl alcohol, tocopherol (vitamin E), arachidyl glucoside, glyceryl stearate, PEK-100 stearate, potassium hydroxide, disodium EDTA, sodium ascorbyl phosphate, fragrance.

OTHER INFORMATION

Protect the product in this container from excessive heat and direct sun.

May stain or damage some fabrics, materials or surfaces.

WARNINGS

For external use only.

DIRECTIONS

Apply liberally 15 minutes before sun exposure.

Reapply:

-After 80 minutes of swimming or sweating.

-Immediately after towel drying.

-At least every 2 hours.

-Children under 6 months of age: Ask a doctor.

-Sun Protection Measures. Spending time in the sun increases your risk of skin cancer and early skin aging. To decrease the risk, regularly use a sunscreen with a broad spectrum SPF value of 15 or higher and other sun protection measures including:

- Limit time in the sun, especially from 10am - 2 pm

Wear long-sleeved shirts, pants, hats and sunglasses.

Directions

Apply liberally 15 minutes before sun exposure.

Reapply:

-After 80 minutes of swimming or sweating.

-Immediately after towel drying.

-At least every 2 hours.

-Children under 6 months of age: Ask a doctor.

-Sun Protection Measures. Spending time in the sun increases your risk of skin cancer and early skin aging. To decrease the risk, regularly use a sunscreen with a broad spectrum SPF value of 15 or higher and other sun protection measures including:

- Limit time in the sun, especially from 10am - 2 pm

Wear long-sleeved shirts, pants, hats and sunglasses.